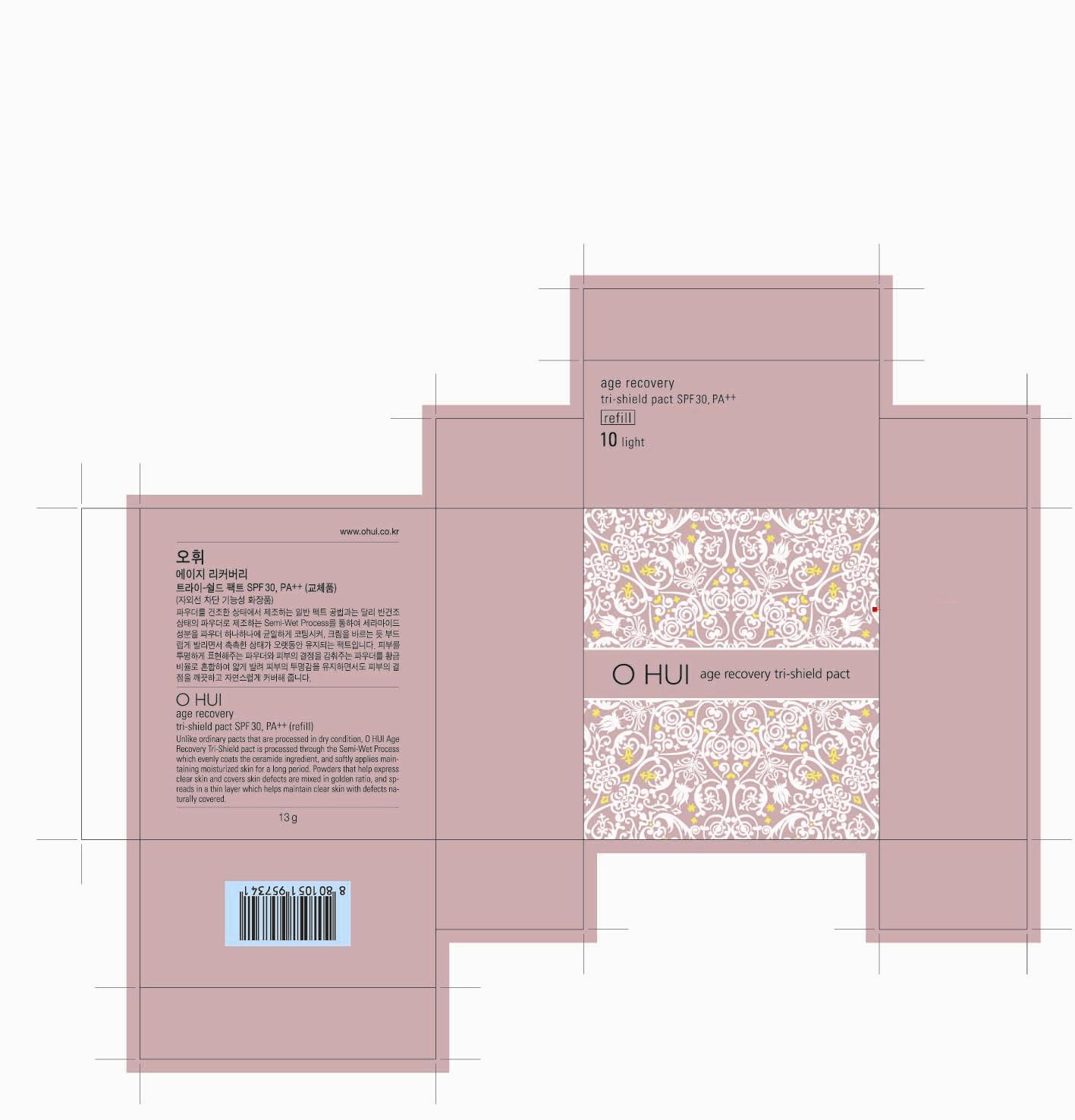 DRUG LABEL: OH Age recovery Tri Shield pact 10
NDC: 53208-551 | Form: POWDER
Manufacturer: LG Household and Healthcare, Inc.
Category: otc | Type: HUMAN OTC DRUG LABEL
Date: 20120514

ACTIVE INGREDIENTS: TITANIUM DIOXIDE 4.9 g/100 g; OCTINOXATE 2 g/100 g
INACTIVE INGREDIENTS: TALC; TRIETHOXYCAPRYLYLSILANE; BORON NITRIDE; DIMETHICONE; MICA; ALUMINUM STARCH OCTENYLSUCCINATE; LAUROYL LYSINE; STEARIC ACID; MAGNESIUM MYRISTATE; MAGNESIUM ALUMINUM SILICATE; TRIETHYLHEXANOIN; FERRIC OXIDE YELLOW; FERROSOFERRIC OXIDE; WATER; CERAMIDE 3; HYDROGENATED SOYBEAN LECITHIN; DIPROPYLENE GLYCOL; ALUMINUM HYDROXIDE; PEG-10 RAPESEED STEROL; PROPYLPARABEN; GLYCERYL MONOSTEARATE; GLYCERIN; POLYDATIN

OHUI AGE RECOVERY TRI SHIELD PACT NO10

ACTIVE INGREDIENT

TITANIUM DIOXIDE 4.9%
OCTINOXATE 2%

WARNINGS AND PRECAUTIONS

For external use only

Keep out of reach of children. Is swallowed, get medical help or contact a
Poison Control Center right away.

WHEN USING

Keep out of eyes. Rinse with water to remove

Stop use if a rash or irritation develops and lasts.